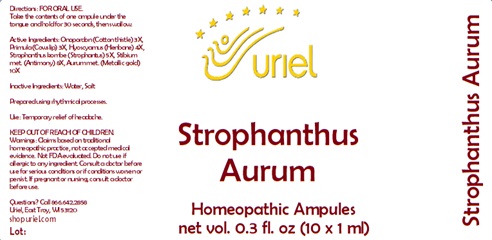 DRUG LABEL: Strophanthus Aurum
NDC: 48951-8216 | Form: LIQUID
Manufacturer: Uriel Pharmacy Inc.
Category: homeopathic | Type: HUMAN OTC DRUG LABEL
Date: 20241219

ACTIVE INGREDIENTS: ONOPORDUM ACANTHIUM FLOWER 3 [hp_X]/1 mL; PRIMULA VERIS FLOWER 3 [hp_X]/1 mL; HYOSCYAMUS NIGER LEAF 4 [hp_X]/1 mL; STROPHANTHUS KOMBE WHOLE 5 [hp_X]/1 mL; ANTIMONY 8 [hp_X]/1 mL; GOLD 10 [hp_X]/1 mL
INACTIVE INGREDIENTS: WATER; SODIUM CHLORIDE

Strophanthus Aurum

INDICATIONS AND USAGE

Directions: FOR ORAL USE.

DOSAGE AND ADMINISTRATION

Take the contents of one ampule
under the tongue and hold for
30 seconds, then swallow.

ACTIVE INGREDIENT

Active Ingredients: Onopordon (Cotton thistle) 3X, Primula (Cowslip) 3X, Hyoscyamus (Henbane) 4X, Strophanthus (Strophantus) 5X, Stibium met. (Antimony) 8X, Aurum (Metallic gold)10X

Inactive Ingredients: Water, Salt

Prepared using rhythmical processes.

PURPOSE

Use: Temporary relief of headache.

KEEP OUT OF REACH OF CHILDREN.

WARNINGS

Warnings: Claims based on traditional homeopathic practice, not accepted medical evidence. Not FDA evaluated. Do not use if allergic to any ingredient. Consult a doctor before use for serious conditions or if conditions worsen or persist. If pregnant or nursing, consult a doctor before use.

QUESTIONS

Questions? Call 866.642.2858 Uriel, East Troy, WI 53120 shopuriel.com Lot: